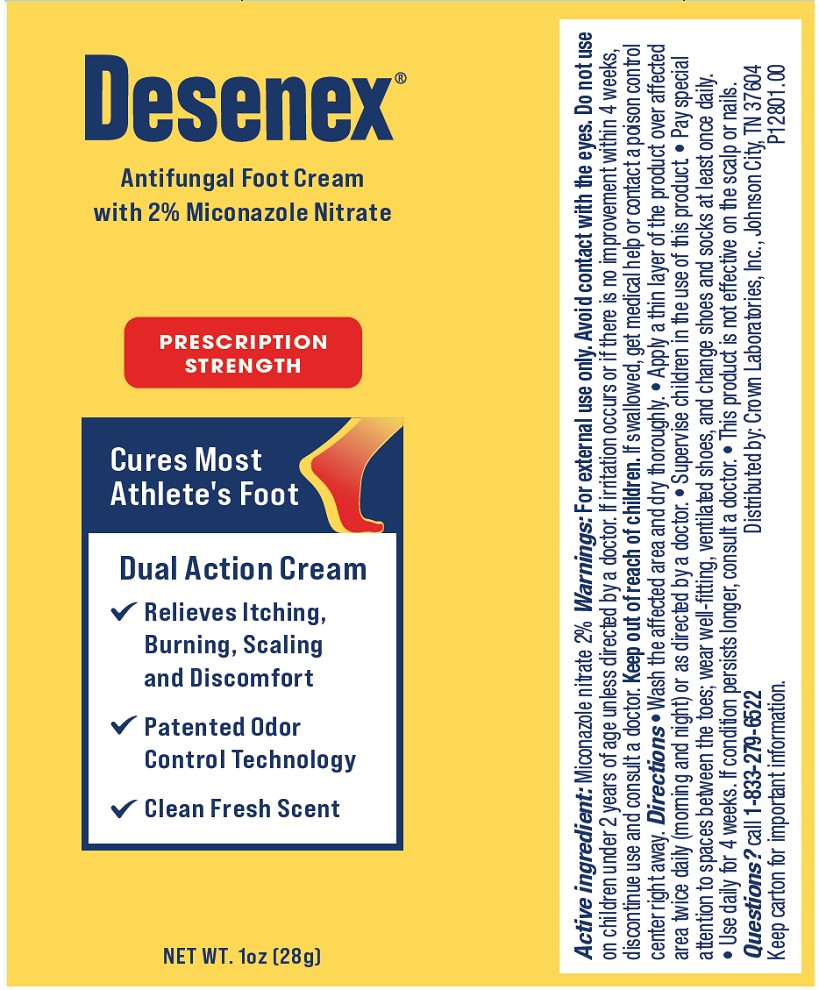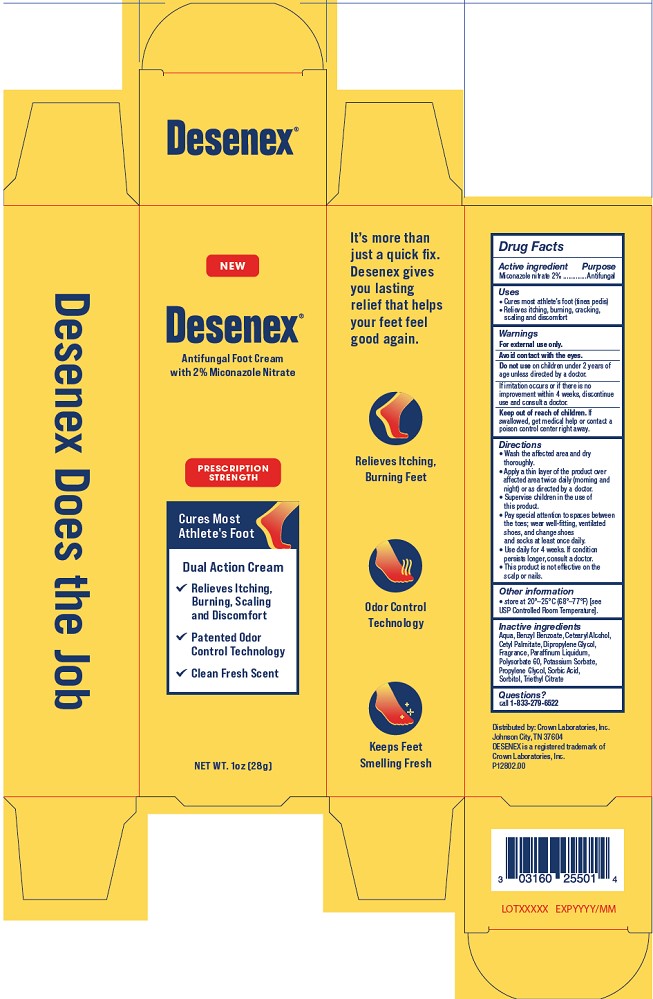 DRUG LABEL: Desenex Antifungal Foot Cream
NDC: 0316-0255 | Form: CREAM
Manufacturer: Crown Laboratories, Inc.
Category: otc | Type: HUMAN OTC DRUG LABEL
Date: 20260112

ACTIVE INGREDIENTS: MICONAZOLE NITRATE 20 mg/1 g
INACTIVE INGREDIENTS: PARAFFINUM LIQUIDUM; PROPYLENE GLYCOL; WATER; POTASSIUM SORBATE; CETYL PALMITATE; DIPROPYLENE GLYCOL; TRIETHYL CITRATE; SORBIC ACID; SORBITOL; BENZYL BENZOATE; POLYSORBATE 60; CETEARYL ALCOHOL

Desenex Antifungal Foot Cream

Active ingredient

Miconazole nitrate 2%

Purpose

Antifungal

Uses

- Cures most athlete's foot (tinea pedis)
- Relieves ithcing, burning, cracking, scaling, and discomfort

Warnings

For external use only.

Avoid contact with eyes.

Do not use

on children under 2 years of age unless directed by a doctor.

Stop use

if irritation occurs or if there is no improvement within 4 weeks, discontinue use and consult a doctor.

Keep out of reach of children.

If swallowed, get medical help or contact a poison control center right away.

Directions

- Wash the affected area and dry thoroughly.
- Apply a thin layer of the product over affected area twice daily (morning and night) or as directed by a doctor.
- Supervise children in the use of this product.
- Pay special attention to spaces between the toes; wear well-fiting, ventilated shoes, and change shoes and socks at least once daily.
- Use daily for 4 weeks. If condition persists longer consult a doctor.
- This product is not effective on the scalp or nails.

Other information

- store at 20°–25°C (68°–77°F) [see USP Controlled Room Temperature].

Inactive ingredients

Aqua, Benzyl Benzoate, Cetearyl Alcohol, Cetyl Palmitate, Dipropylene Glycol, Fragrance, Paraffinum Liquidum, Polysorbate 60, Potassium Sorbate, Propylene Glycol, Sorbic Acid, Sorbitol, Triethyl Citrate

Questions?

call 1-833-279-6522

Desenex Cream Tube

Desenex

Antifungal Foot Cream

with 2% Miconazole Nitrate

PRESCRIPTION STRENGTH

Cures Most Athlete's Foot

Dual Action Cream

Relieves Itching, Burning, Scaling, and Discomfort

Patented Odor Control Technology

Clean Fresh Scent

NET WT. 1oz (28g)

Distributed by: Crown Laboratories, Inc. Johnson City, TN 36704

P12801.00

Desenex Cream Carton

Desenex

Antifungal Foot Cream

with 2% Miconazole Nitrate

PRESCRIPTION STRENGTH

Cures Most Athlete's Foot

Dual Action Cream

Relieves Itching, Burning, Scaling, and Discomfort

Patented Odor Control Technology

Clean Fresh Scent

NET WT. 1oz (28g)

Distributed by: Crown Laboratories, Inc. Johnson City, TN 37604

Desenex is a registered trademark of Crown Laboratories, Inc.

P12802.00